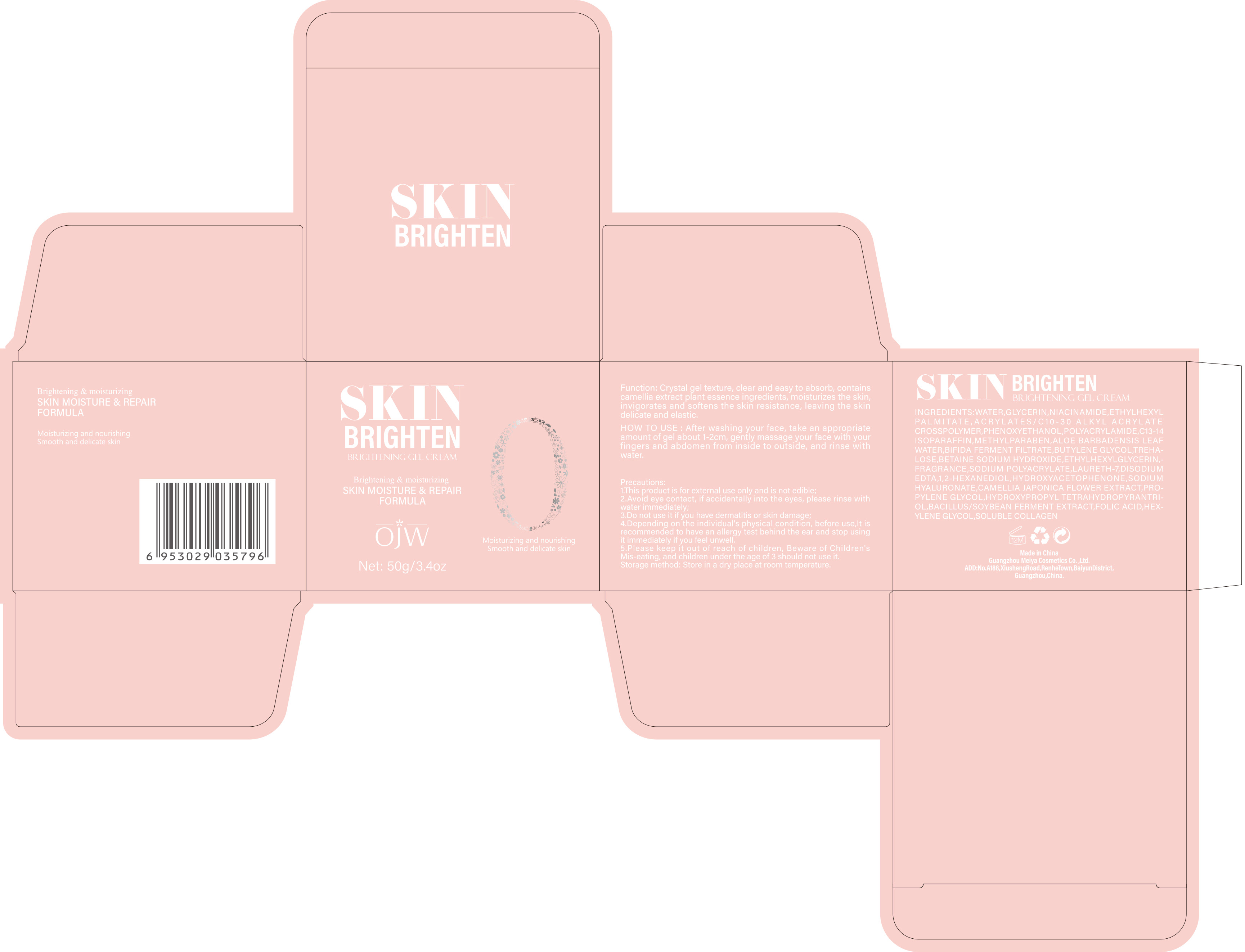 DRUG LABEL: gel cream
NDC: 84673-011 | Form: EMULSION
Manufacturer: Guangzhou Meiya Cosmetics Co. ,Ltd.
Category: otc | Type: HUMAN OTC DRUG LABEL
Date: 20240927

ACTIVE INGREDIENTS: NIACINAMIDE 50 mg/1 g
INACTIVE INGREDIENTS: GLYCERIN 5 mg/1 g; C13-14 ISOPARAFFIN 0.175 mg/1 g; LAURETH-7 0.035 mg/1 g; PHENOXYETHANOL 0.45 mg/1 g; ETHYLHEXYLGLYCERIN 0.05 mg/1 g; METHYLPARABEN 0.15 mg/1 g; HYDROXYACETOPHENONE 0.00036 mg/1 g; BUTYLENE GLYCOL 0.11 mg/1 g; BETAINE 0.11 mg/1 g; SODIUM HYDROXIDE 0.1 mg/1 g; FOLIC ACID 0.000002 mg/1 g; HYDROXYPROPYL TETRAHYDROPYRANTRIOL 0.000005 mg/1 g; TREHALOSE 0.11 mg/1 g; ETHYLHEXYL PALMITATE 1 mg/1 g; 1,2-HEXANEDIOL 0.00048 mg/1 g; HEXYLENE GLYCOL 0.000001 mg/1 g; WATER 88.56 mg/1 g

PURPOSE

Function: Crystal gel texture, clear and easy to absorb, contains camellia extract plant essence ingredients, moisturizes the skin, invigorates and softens the skin resistance, leaving the skin delicate and elastic.

INDICATIONS AND USAGE

HOW TO USE : After washing your face, take an appropriate amount of gel about 1-2cm, gently massage your face with your fingers and abdomen from inside to outside, and rinse with water.

WARNINGS

This product is for external use only and is not edible

STOP USE

1. Avoid eye contact, if accidentally into the eyes, please rinse with water immediately;

2. Do not use it if you have dermatitis or skin damage;

3. Depending on the individual's physical condition, before use,It is recommended to have an allergy test behind the ear and stop using it immediately if you feel unwell.

DO NOT USE

1. Avoid eye contact, if accidentally into the eyes, please rinse with water immediately;

2. Do not use it if you have dermatitis or skin damage;

3. Depending on the individual's physical condition, before use,It is recommended to have an allergy test behind the ear and stop using it immediately if you feel unwell.

WHEN USING

1. This product is for external use only and is not edible;

2. Avoid eye contact, if accidentally into the eyes, please rinse with water immediately;

3. Do not use it if you have dermatitis or skin damage;

4. Depending on the individual's physical condition, before use,It is recommended to have an allergy test behind the ear and stop using it immediately if you feel unwell.

5. Please keep it out of reach of children, Beware of Children's Mis-eating, and children under the age of 3 should not use it.

KEEP OUT OF REACH OF CHILDREN

Please keep it out of reach of children, Beware of Children's Mis-eating, and children under the age of 3 should not use it.